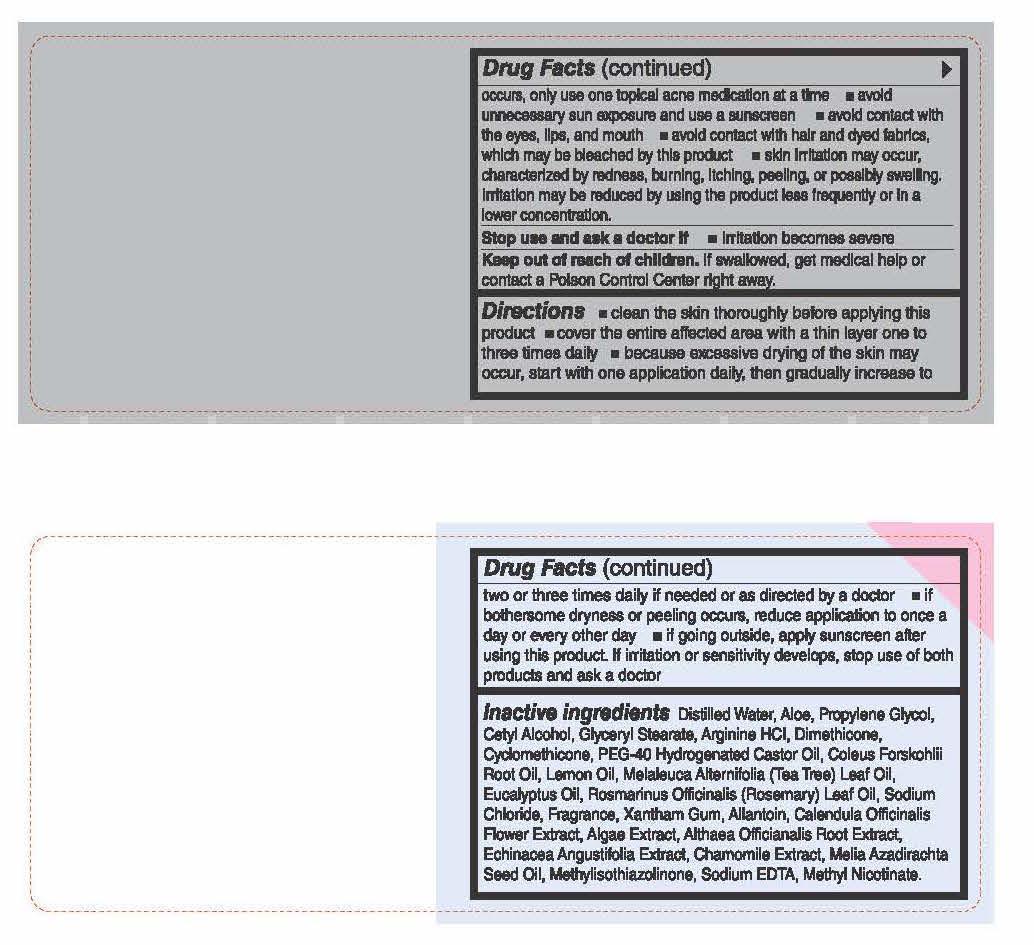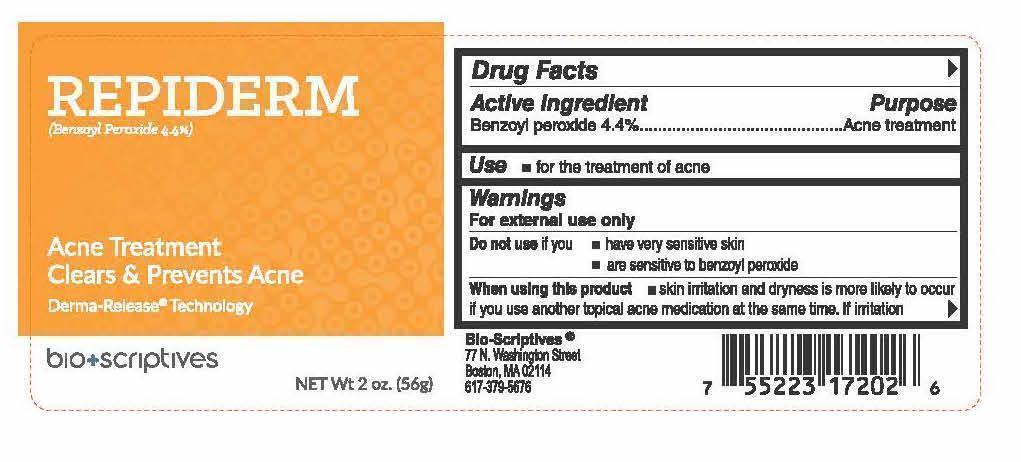 DRUG LABEL: Bio-Scriptives Repiderm
NDC: 60608-012 | Form: CREAM
Manufacturer: BioChemics, Inc.
Category: otc | Type: HUMAN OTC DRUG LABEL
Date: 20150310

ACTIVE INGREDIENTS: BENZOYL PEROXIDE 3.29 g/56 g
INACTIVE INGREDIENTS: water; ALOE VERA LEAF; PROPYLENE GLYCOL; CETYL ALCOHOL; GLYCERYL MONOSTEARATE; ARGININE HYDROCHLORIDE; DIMETHICONE; CYCLOMETHICONE; HYDROGENATED CASTOR OIL; COLEUS FORSKOHLII ROOT OIL; LEMON OIL; MELALEUCA ALTERNIFOLIA LEAF; EUCALYPTUS OIL; ROSEMARY OIL; SODIUM CHLORIDE; XANTHAN GUM; ALLANTOIN; AZADIRACHTIN; ALTHAEA OFFICINALIS ROOT; CALENDULA OFFICINALIS FLOWERING TOP; ASCOPHYLLUM NODOSUM; ECHINACEA ANGUSTIFOLIA; CHAMOMILE; METHYLISOTHIAZOLINONE; EDETATE SODIUM; METHYL NICOTINATE

Drug Facts

Active Ingredients

4.4% Benzoyl Peroxide

Purpose

Acne Treatment

Uses

■ for the treatment of acne

WARNINGS

For external use only

Do not use if you

■ have very sensative skin

■ if you are sensative to benzoly peroxide

When using this product

■ skin irritation and dryness is more likely to occur if you use another topical acne medication at the same time. If irritation occurs, only use one topical acne medication at a time. ■ avoid unnecessary sun exposure and use a sunscreen. ■ avoid contact with eyes, lips, and mouth. ■ avoid contact with hair and dyed fabrics which may be bleached by this product. ■ skin irritation may occur, characterized by redness, burning, itching, peeling, or possibly swelling. Irritation may be reduced by using the product less frequenly or in a lower concentration.

Stop use and ask a doctor if ■ irritation becomes severe

KEEP OUT OF REACH OF CHILDREN

If swallowed, get medical help or contact a Poison Control Center right away.

Directions

■ clean the skin thoroughly before applying this product ■ cover the entire affected area with a think layer one to three times daily ■ because excessive drying of the skin may occur, start with one application daily, then gradually increase to two or three times daily if needed or as directed by a doctor ■ if bothersome dryness or peelinig occurs, reduce application to once a day or every other day ■ if going outside, apply sunscreen after using this product. If irritation or sensitivity develops, stop use of both products and ask a doctor.

Inactive Ingredients

Distilled Water, Aloe, Propylene Glycol, Cetyl Alcohol, Glyceryl Monostearate, Arginine HCI, Dimethicone, Cyclomethicone, PEG-40 Hydrogenated Castor Oil, Coleus Forskohlii Oil, Lemon Oil, Melaleuca Alternifolia (Tea Tree) Leaf Oil, Eucalyptus Oil, Rosmarius Officianalis (Rosemay) Leaf Oil, Sodium Chloride, Fragrance, Xanthan Gum, Allantoin, Calendula Officinalis Flower Extract, Algae Extract, Althaea Officianalis Root Extract, Echinacea Augustifolia Extract, Chamomile Extract, Melia Azadirachta See Oil, Methylisothiazolinone, Sodium EDTA, Methyl Nicotinate.

QUESTIONS

BioScriptives™

77 N. Washington Street

Boston, MA 02114

617-379-5676